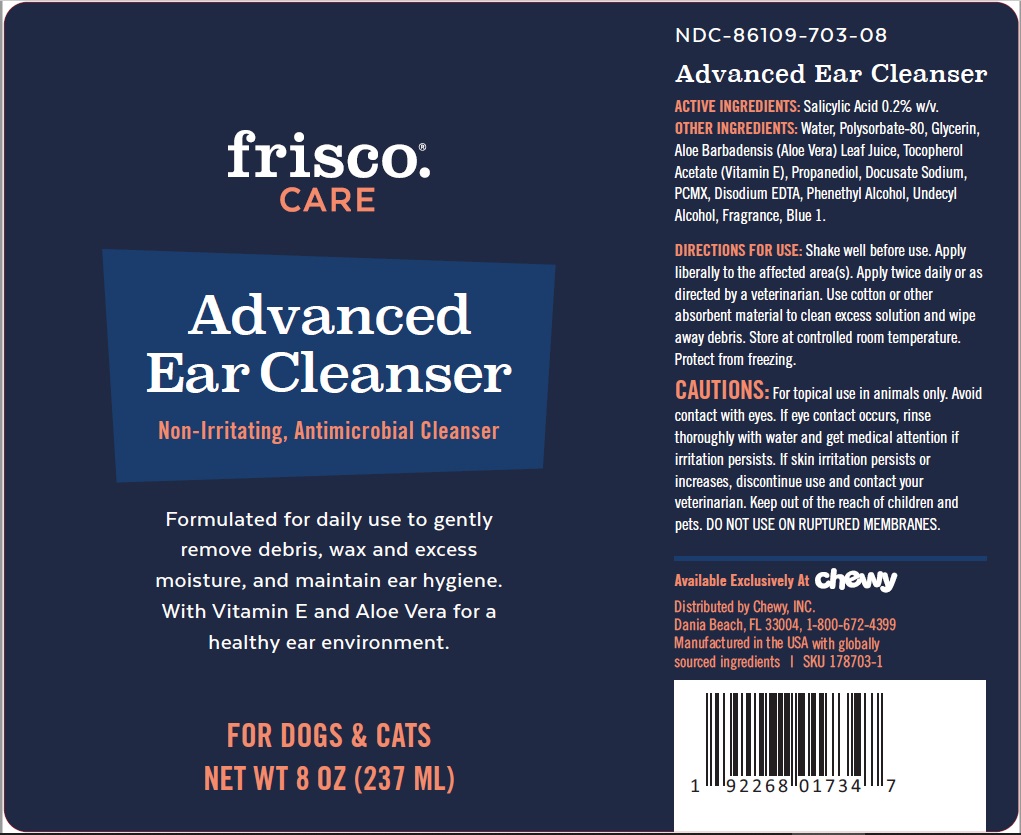 DRUG LABEL: frisco CARE Advanced Ear Cleanser
NDC: 86109-703 | Form: LIQUID
Manufacturer: Chewy, Inc.
Category: animal | Type: OTC ANIMAL DRUG LABEL
Date: 20201127

ACTIVE INGREDIENTS: SALICYLIC ACID 2 mg/1 mL
INACTIVE INGREDIENTS: WATER; POLYSORBATE 80; GLYCERIN; ALOE VERA LEAF; .ALPHA.-TOCOPHEROL ACETATE; PROPANEDIOL; DOCUSATE SODIUM; CHLOROXYLENOL; EDETATE DISODIUM ANHYDROUS; PHENYLETHYL ALCOHOL; UNDECYL ALCOHOL; FD&C BLUE NO. 1

frisco.® CARE Advanced Ear Cleanser

ACTIVE INGREDIENTS: Salicylic Acid 0.2% w/v.

PURPOSE

Antimicrobial Cleanser

INDICATIONS AND USAGE

Formulated for daily use to gently remove debris, wax and excess moisture, and maintain ear hygiene.
With Vitamin E and Aloe Vera for a healthy ear environment.

WARNINGS

CAUTIONS: For topical use in animals only. Avoid contact with eyes. If eye contact occurs, rinse thoroughly with water and get medical attention if irritation persists. If skin irritation persists or increases, discontinue use and contact your veterinarian. Keep out of the reach of children and
pets. DO NOT USE ON RUPTURED MEMBRANES.

DOSAGE AND ADMINISTRATION

DIRECTIONS FOR USE: Shake well before use. Apply liberally to the affected area(s). Apply twice daily or as directed by a veterinarian. Use cotton or other absorbent material to clean excess solution and wipe away debris. Store at controlled room temperature. Protect from freezing.

INACTIVE INGREDIENT

OTHER INGREDIENTS: Water, Polysorbate-80, Glycerin, Aloe Barbadensis (Aloe Vera) Leaf Juice, Tocopherol Acetate (Vitamin E), Propanediol, Docusate Sodium, PCMX, Disodium EDTA, Phenethyl Alcohol, Undecyl Alcohol, Fragrance, Blue 1.

Non-Irritating, Antimicrobial Cleanser

FOR DOGS & CATS

Available Exclusively At Chewy

Distributed by Chewy, INC.
Dania Beach, FL 33004
1-800-672-4399

Manufactured in the USA with globally sourced ingredients